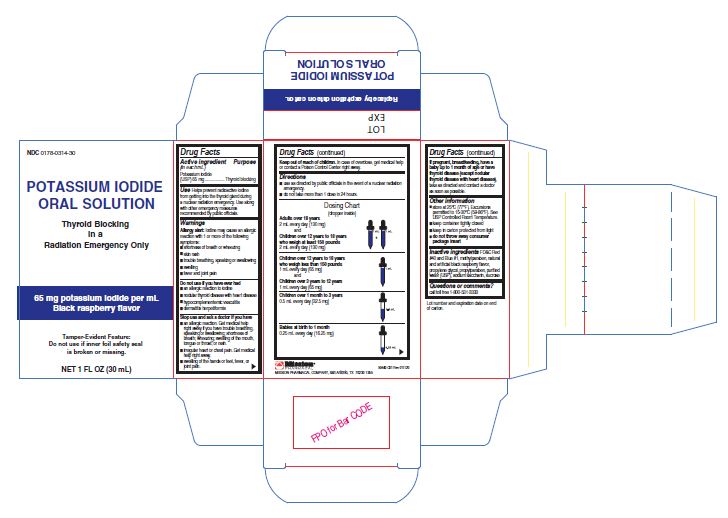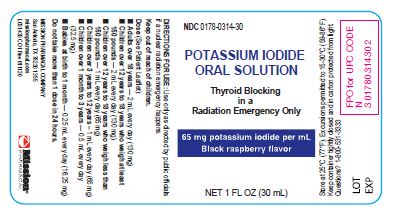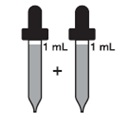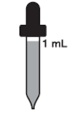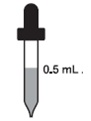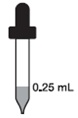 DRUG LABEL: POTASSIUM IODIDE
NDC: 0178-0314 | Form: SOLUTION
Manufacturer: Mission Pharmacal Company
Category: otc | Type: HUMAN OTC DRUG LABEL
Date: 20230110

ACTIVE INGREDIENTS: POTASSIUM IODIDE 65 mg/1 mL
INACTIVE INGREDIENTS: FD&C RED NO. 40; FD&C BLUE NO. 1; METHYLPARABEN; BLACK RASPBERRY; PROPYLENE GLYCOL; PROPYLPARABEN; WATER; SUCROSE; SACCHARIN SODIUM

Potassium Iodide Oral Solution - potassium iodide oral solution

Active Ingredient
Potassium iodide (USP) 65 mg

Purpose
Thyroid blocking

Uses
Helps prevent radioactive iodine from getting into the thyroid gland during a nuclear radiation emergency. Use along with other emergency measures recommended by public officials.

Warnings

Allergy alert: Iodine may cause an allergic reaction with 1 or more of the following symptoms:

- shortness of breath or wheezing
- skin rash
- trouble breathing, speaking or swallowing
- swelling
- fever and joint pain

Do not use if you have ever had
- an allergic reaction to iodine
- nodular thyroid disease with heart disease
- hypocomplementemic vasculitis
- dermatitis herpetiformis

Stop use and ask a doctor if you have
- an allergic reaction. Get medical help right away if you have trouble breathing, speaking or swallowing; shortness of breath; wheezing; swelling of the mouth, tongue or throat; or rash.
- irregular heart or chest pain. Get medical help right away.
- swelling of the hands or feet, fever, or joint pain.

Keep Out of Reach of Children.

In case of overdose, get medical help or contact a Poison Control Center right away.

Directions

- use as directed by public officials in the event of a nuclear radiation emergency.
- do not take more than 1 dose in 24 hours.

Dosing Chart
(dropper inside)

Adults over 18 years
2 mL every day (130 mg)
and
Children over 12 years to 18 years
who weigh at least 150 pounds
2 mL every day (130 mg)

Children over 12 years to 18 years
who weigh less than 150 pounds
1 mL every day (65 mg)
and
Children over 3 years to 12 years
1 mL every day (65 mg)

Children over 1 month to 3 years
0.5 mL every day (32.5 mg)

Babies at birth to 1 month
0.25 mL every day (16.25 mg)

PREGNANCY OR BREAST FEEDING

If pregnant, breastfeeding, have a baby up to 1 month of age or have thyroid disease (except nodular thyroid disease with heart disease), take as directed and contact a doctor as soon as possible.

Other Information

- store at 25°C (77°F). Excursions permitted to 15-30°C (59-86°F). See USP Controlled Room Temperature.
- keep container tightly closed
- keep in carton protected from light
- do not throw away consumer package insert

Inactive ingredients
FD&C Red #40 and Blue #1, methylparaben, natural and artificial black raspberry flavor, propylene glycol, propylparaben, purified water (USP), sodium saccharin, sucrose

Questions or Comments?
call toll free 1-800-531-3333

Consumer Package Insert

POTASSIUM IODIDE ORAL SOLUTION
(Potassium Iodide Oral Solution, 1 mL = 65 mg)
(Abbreviated KI)

Take potassium iodide (KI) only when public officials tell you. In a nuclear radiation emergency, radioactive iodine could be released into the air. KI protects only the thyroid gland from uptake of radioactive iodine. Therefore, KI should be used along with other emergency measures that will be recommended to you by public officials.

If you are told to take this medicine, take it one time every 24 hours. Do not take it more often. More KI will not help you. Too much KI may increase the chances of side effects. Do not take this medicine if you know you are allergic to iodine (see SIDE EFFECTS below).

DESCRIPTION:

Each milliliter (1 mL) of Potassium Iodide Oral Solution contains 65 mg of potassium iodide (USP) in a black raspberry-flavored solution. Inactive ingredients are: FD&C Red #40 and Blue #1, methylparaben, natural and artificial black raspberry flavor, propylene glycol, propylparaben, purified water (USP), sodium saccharin, sucrose.

INDICATIONS:

Potassium Iodide Oral Solution is a thyroid blocking medicine that is used in a nuclear radiation emergency only.

DIRECTIONS FOR USE:

Use only as directed by public officials if a nuclear radiation emergency happens.

Dose:

Adults over 18 years 2 mL every day (130 mg)

Children over 12 years to 18 years 2 mL every day (130 mg)
who weigh at least 150 pounds

Children over 12 years to 18 years 1 mL every day (65 mg)
who weigh less than 150 pounds

Children over 3 years to 12 years 1 mL every day (65 mg)

Children over 1 month to 3 years 0.5 mL every day (32.5 mg)

Babies at birth to 1 month 0.25 mL every day (16.25 mg)

Take KI every day (every 24 hours) as directed by public officials. Do not take more than 1 dose in 24 hours. More will not help you. Too much medicine may increase the chances of side effects.

PREGNANCY OR BREAST FEEDING

Pregnant or breastfeeding women, or babies under 1 month of age: Take as directed above and call a doctor as soon as possible. Repeat dosing should be avoided. It is recommended that thyroid function be checked in babies less than 1 month of age that take KI. Women who are pregnant or breastfeeding should also be checked by a doctor if repeat dosing is necessary. Although these precautions should be taken, the benefits of short-term use of KI to block uptake of radioactive iodine by the thyroid gland far exceed its chances of side effects.

Patients with thyroid disease: If you have both a nodular thyroid condition such as multinodular goiter with heart disease, you should not take KI. Patients with other thyroid conditions may take KI as directed above, but call a doctor if you need to take KI for more than a few days.

WARNING:

People who are allergic to iodine, have dermatitis herpetiformis or hypocomplementemic vasculitis, or have nodular thyroid disease with heart disease should not take KI. Keep out of the reach of children. In case of an allergic reaction (difficulty breathing, speaking or swallowing; wheezing; shortness of breath or swelling of the mouth or throat), call 911 or get medical care right away. In case of overdose, get medical help or call a Poison Control Center right away.

HOW POTASSIUM IODIDE WORKS:

Certain forms of iodine help your thyroid gland work right. Most people get the iodine they need from foods like iodized salt or fish. The thyroid can “store” or hold only a certain amount of iodine.

In a nuclear radiation emergency, radioactive iodine may be released in the air. This material may be breathed or swallowed. It may enter the thyroid gland and damage it. The damage would probably not show itself for years. Children are most likely to have thyroid damage.

If you take KI, it will block or reduce the chances that radioactive iodine will enter your thyroid gland.

WHO SHOULD NOT TAKE POTASSIUM IODIDE:

People should avoid KI if they are allergic to iodine, have dermatitis herpetiformis or hypocomplementemic vasculitis, or have nodular thyroid disease with heart disease, because these conditions may increase the chances of side effects to iodine.

HOW AND WHEN TO TAKE POTASSIUM IODIDE:

KI should be taken as soon as possible after public officials tell you. If you are told to repeat the dose, you should take the second dose 24 hours after the first dose. Do not take it sooner. More KI will not help you because the thyroid can “hold” only certain amounts of iodine. Taking more than 1 dose per day will increase the chances of side effects. The public officials will tell you how many days to take KI. You should take KI until the chances of major exposure to radioactive iodine by breathing or swallowing stops.

SIDE EFFECTS:

Short-term use of KI at the recommended dose is safe. You should not take this drug for longer than you are told.

Possible side effects include: swelling of the salivary glands, nausea, vomiting, diarrhea, stomach ache, fever, headache, metallic taste, and allergic reactions. Allergic reaction can include

- skin rashes such as hives
- swelling of various parts of the body such as the face, lips, tongue, throat, hands or feet
- fever with joint pain
- trouble breathing, speaking or swallowing
- wheezing or shortness of breath

Get medical attention right away if you have trouble breathing, speaking or swallowing; wheezing; shortness of breath; or swelling of the mouth, tongue or throat.

Taking iodide, in rare cases, may cause overactivity of the thyroid gland, underactivity of the thyroid gland, or enlargement of the thyroid gland (goiter). Symptoms of an overactive thyroid gland may include an irregular heart beat and chest pain. Patients with thyroid disease are more likely to get these side effects. Babies under 1 month of age are more likely to get an underactive thyroid gland (hypothyroidism).

WHAT TO DO IF SIDE EFFECTS OCCUR:

Stop taking KI and call a doctor if you have one or more of the following symptoms:
- swelling of the face, hands or feet
- fever and joint pain
- skin rash

Stop taking KI and get medical help right away if you have one or more of the following symptoms:
- trouble breathing, speaking or swallowing
- shortness of breath or wheezing
- swelling of the lips, tongue or throat
- irregular heart beat or chest pain

INACTIVE INGREDIENTS:

FD&C Red #40 and Blue #1, methylparaben, natural and artificial black raspberry flavor, propylene glycol, propylparaben, purified water (USP), sodium saccharin, sucrose.

HOW SUPPLIED:

Potassium Iodide Oral Solution is supplied in 1 oz (30 mL) bottles. Each mL contains 65 mg potassium iodide. Store at 25°C (77°F). Excursions permitted to 15-30°C (59-86°F). [See USP Controlled Room Temperature.] Keep container tightly closed and in carton, protected from light.

MISSION PHARMACAL COMPANY
San Antonio, TX 78230 1355

PISP-001 C01 Rev 011120

PACKAGE LABEL

Principal Display Panel - carton

PACKAGE LABEL

Principal Display Panel - bottle